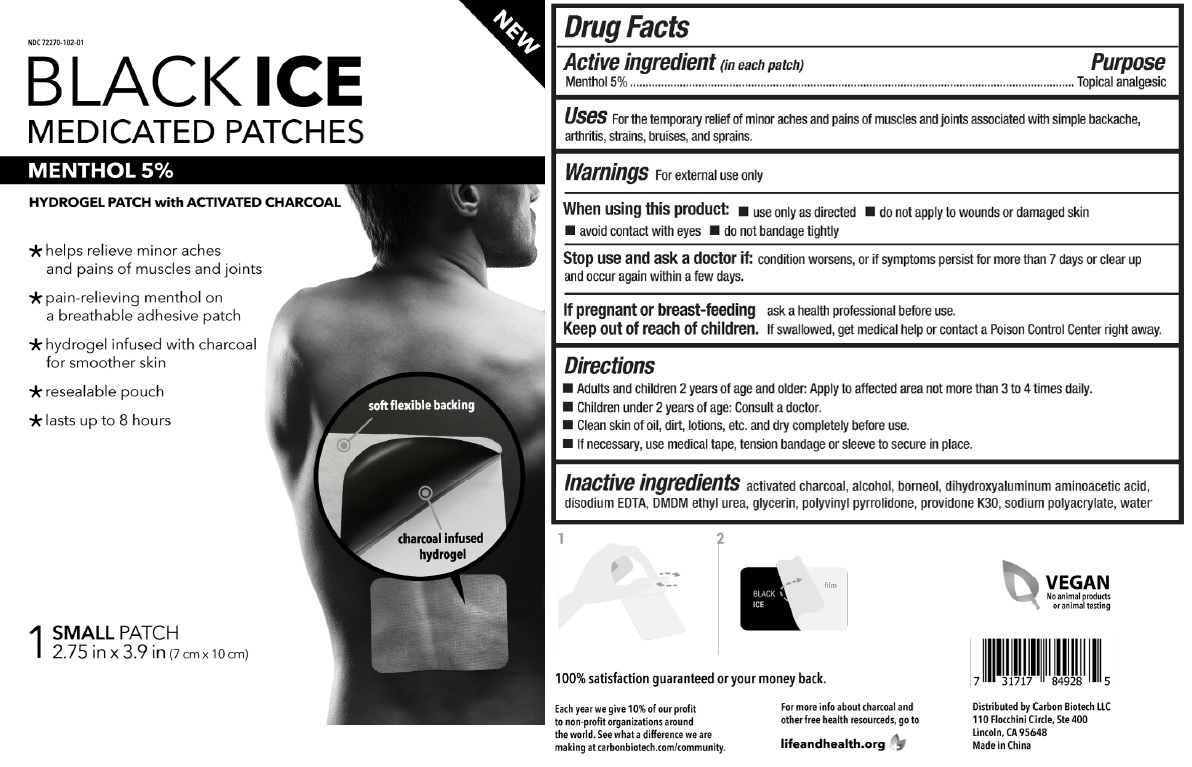 DRUG LABEL: BLACK ICE MEDICATED PATCHES
NDC: 72411-102 | Form: PATCH
Manufacturer: Carbon Biotech Llc
Category: otc | Type: HUMAN OTC DRUG LABEL
Date: 20180716

ACTIVE INGREDIENTS: MENTHOL, UNSPECIFIED FORM 0.156 g/1 1
INACTIVE INGREDIENTS: ACTIVATED CHARCOAL; ALCOHOL; BORNEOL; DIHYDROXYALUMINUM AMINOACETATE; EDETATE DISODIUM ANHYDROUS; DMDM HYDANTOIN; GLYCERIN; POVIDONE K30; SODIUM POLYACRYLATE (2500000 MW); WATER

BLACK ICE MEDICATED PATCHES

Active ingredient (in each patch)

Menthol 5%

Purpose

Topical analgesic

Uses

For the temporary relief of minor aches and pains of muscles and joints associated with simple backache, arthritis, strains, bruises, and sprains.

Warnings

For external use only

When using this product: • use only as directed • do not apply to wounds or damaged skin • avoid contact with eyes • do not bandage tightly

Stop use and ask a doctor if: condition worsens, or if symptoms persist for more than 7 days or clear up and occur again within a few days.

If pregnant or breast-feeding ask a health professional before use.

Keep out of reach of children. If swallowed, get medical help or contact a Poison Control Center right away.

Directions

- Adults and children 2 years of age and older: Apply to affected area not more than 3 to 4 times daily.

- Children under 2 years of age: Consult a doctor.

- Clean skin of oil, dirt, lotions, etc. and dry completely before use.

- If necessary, use medical tape, tension bandage or sleeve to secure in place.

Inactive ingredients

activated charcoal, alcohol, borneol, dihydroxyaluminum aminoacetic acid, disodium EDTA, DMDM ethyl urea, glycerin, polyvinyl pyrrolidone povidone K30, sodium polyacrylate, water

HYDROGEL PATCH with ACTIVATED CHARCOAL

* helps relieve minor aches and pains of muscles and joints

* pain-relieving menthol on a breathable adhesive patch

* hydrogel infused with charcoal for smoother skin

* resealable pouch

* lasts up to 8 hours

VEGAN

No animal products or animal testing

For more info about charcoal and other free health resources, go to lifeandhealth.org

Distributed by Carbon Biotech LLC

110 Flocchini Circle, Ste 400

Lincoln, CA 95648

Made in China